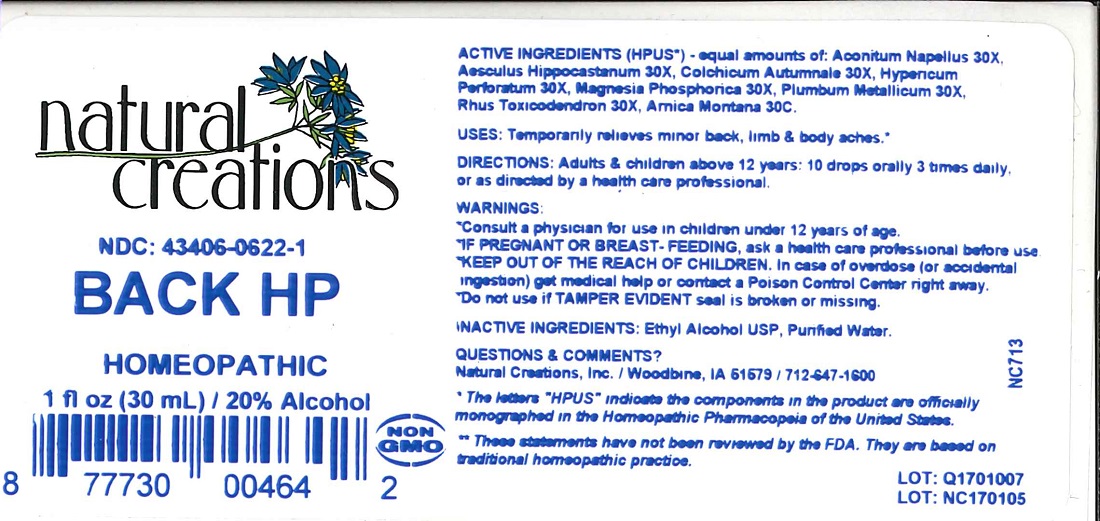 DRUG LABEL: BACK HP
NDC: 43406-0622 | Form: LIQUID
Manufacturer: Natural Creations, Inc.
Category: homeopathic | Type: HUMAN OTC DRUG LABEL
Date: 20251113

ACTIVE INGREDIENTS: ACONITUM NAPELLUS 30 [hp_X]/1 mL; HORSE CHESTNUT 30 [hp_X]/1 mL; COLCHICUM AUTUMNALE BULB 30 [hp_X]/1 mL; HYPERICUM PERFORATUM 30 [hp_X]/1 mL; MAGNESIUM PHOSPHATE, DIBASIC TRIHYDRATE 30 [hp_X]/1 mL; LEAD 30 [hp_X]/1 mL; TOXICODENDRON PUBESCENS LEAF 30 [hp_X]/1 mL; ARNICA MONTANA 30 [hp_C]/1 mL
INACTIVE INGREDIENTS: ALCOHOL; WATER

BACK HP

ACTIVE INGREDIENT

ACTIVE INGREDIENTS (HPUS*) - equal amounts of: Aconitum Napellus 30X, Aesculus Hippocastanum 30X, Colchicum Autumnale 30X, Hypericum Perforatum 30X, Magnesia Phosphorica 30X, Plumbum Metallicum 30X, Rhus Toxicodendron 30X, Arnica Montana 30C.

PURPOSE

USES: Temporarily relieves minor back, limb, & body aches.**

INDICATIONS AND USAGE

USES: Temporarily relieves minor back, limb, & body aches.**

DOSAGE AND ADMINISTRATION

DIRECTIONS: Adults & children above 12 years: 10 drops orally 3 times daily, or as directed by a health care professional.

WARNINGS:

* Consult a physician for use in children under 12 years of age.

* IF PREGNANT OR BREAST-FEEDING, ask a health care professional before use.

* KEEP OUT OF THE REACH OF CHILDREN. In case of overdose (or accidental ingestion) get medical help or contact a Poison Control Center right away.

WARNINGS:

* Consult a physician for use in children under 12 years of age.

* IF PREGNANT OR BREAST-FEEDING, ask a health care professional before use.

* KEEP OUT OF THE REACH OF CHILDREN. In case of overdose (or accidental ingestion) get medical help or contact a Poison Control Center right away.

* Do not use if TAMPER EVIDENT seal is broken or missing.

INACTIVE INGREDIENTS: Ethyl Alcohol USP, Purified Water.

QUESTIONS & COMMENTS?:

Natural Creations, Inc. / Woodbine, IA 51579 / 712-647-1600

REFERENCES

* The letters "HPUS" indicate the components in the product are officially monographed in the Homeopathic Pharmacopeia of the United States.

** These statements have not been reviewed by the FDA. They are based on traditional homeopathic practice.

LOT:

PACKAGE LABEL

NDC: 43406-0622-1

BACK HP

HOMEOPATHIC

1 fl oz (30 mL) / 20% Alcohol

UPC: 877730004642 NON GMO Logo